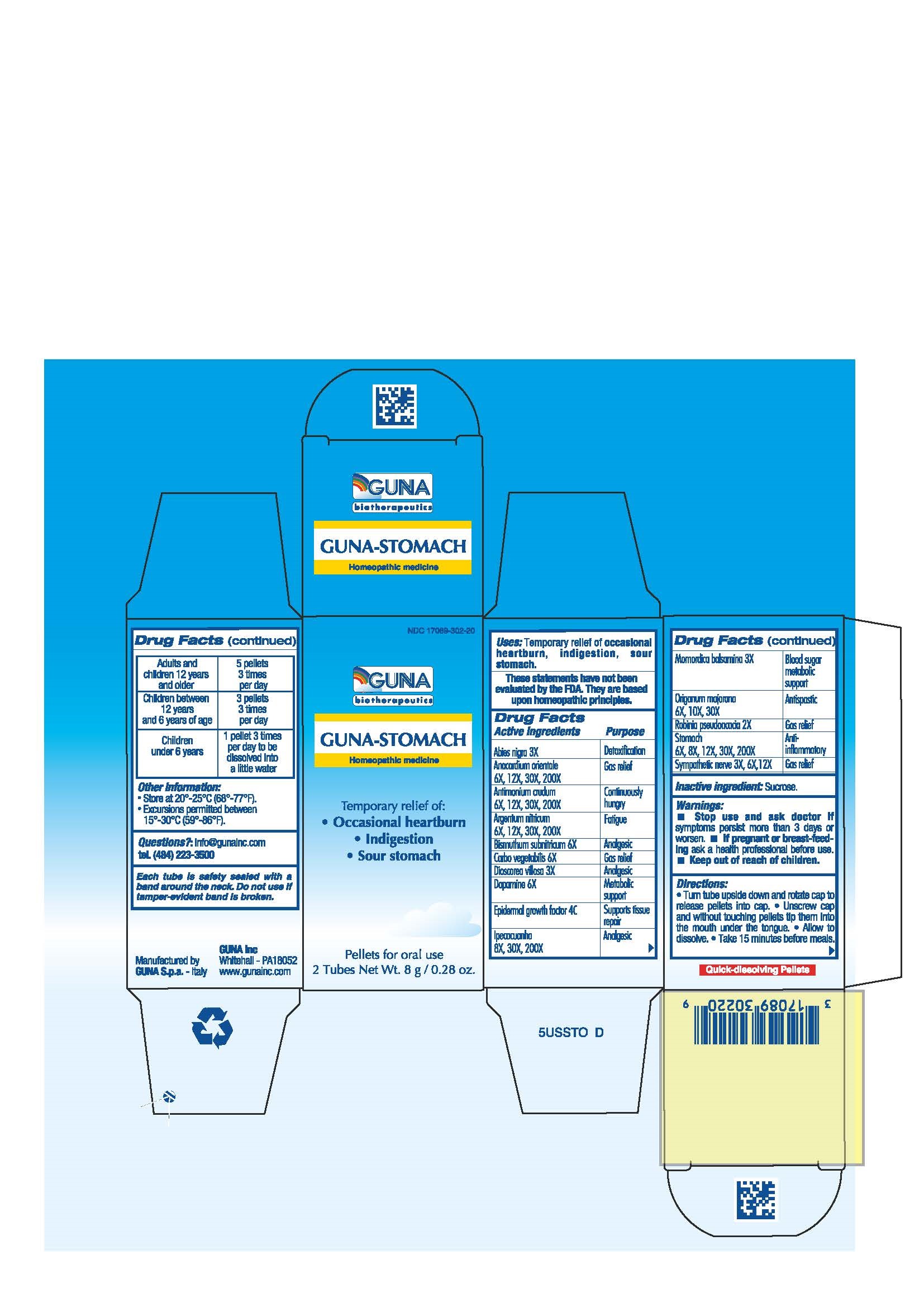 DRUG LABEL: GUNA-STOMACH
NDC: 17089-302 | Form: PELLET
Manufacturer: Guna spa
Category: homeopathic | Type: HUMAN OTC DRUG LABEL
Date: 20221115

ACTIVE INGREDIENTS: PICEA MARIANA RESIN 3 [hp_X]/4 g; SEMECARPUS ANACARDIUM JUICE 30 [hp_X]/4 g; ANTIMONY TRISULFIDE 30 [hp_X]/4 g; SILVER NITRATE 30 [hp_X]/4 g; BISMUTH SUBNITRATE 6 [hp_X]/4 g; ACTIVATED CHARCOAL 6 [hp_X]/4 g; IPECAC 30 [hp_X]/4 g; DIOSCOREA VILLOSA ROOT 3 [hp_X]/4 g; DOPAMINE 6 [hp_X]/4 g; HUMAN EPIDERMAL GROWTH FACTOR 4 [hp_C]/4 g; MOMORDICA BALSAMINA IMMATURE FRUIT 3 [hp_X]/4 g; OREGANO 10 [hp_X]/4 g; ROBINIA PSEUDOACACIA BARK 2 [hp_X]/4 g; SUS SCROFA STOMACH 30 [hp_X]/4 g; SUS SCROFA SYMPATHETIC NERVE 6 [hp_X]/4 g
INACTIVE INGREDIENTS: SUCROSE 3.5 g/4 g

GUNA-STOMACH

ACTIVE INGREDIENTS/PURPOSE

ABIES NIGRA 3X DETOXIFICATION
ANACARDIUM ORIENTALE 6X, 12X, 30X, 200X GAS RELIEF
ANTIMONIUM CRUDUM 6X, 12X, 30X, 200X CONTINUOUSLY HUNGRY
ARGENTUM NITRICUM 6X, 12X, 30X, 200X FATIGUE
BISMUTHUM SUBNITRICUM 6X ANALGESIC
CARBO VEGETALIS 6X GAS RELIEF
DIOSCOREA VILLOSA 3X ANALGESIC
DOPAMINE 6X METABOLIC SUPPORT
EPIDERMAL GROWTH FACTOR 4C SUPPORT TISSUE REPAIR
IPECACUANHA 8X, 30X, 200X ANALGESIC
MOMORDICA BALSAMINA 3X BLOOD SUGAR METABOLIC SUPPORT
ORIGANUM MAJORANA 6X, 10X, 30X ANTISPASTIC
ROBINIA PSEUDOACACIA 2X GAS RELIEF
STOMACH 6X, 8X, 12X, 30X, 200X ANTI-INFLAMMATORY
SYMPATHETIC NERVE 3X, 6X, 12X GAS RELIEF

USES

Temporary relief of:

- occasional heartburn
- indigestion
- sour stomach

WARNINGS

- Stop use and ask doctor if symptoms persist more than 3 days or worsen.
- If pregnant or breast-feeding ask a health professional before use.
- Keep out of reach of children.

PREGNANCY

If pregnant or breast-feeding ask a health professional before use.

WARNINGS

Keep out of reach of children

DIRECTIONS

- Turn tube upside down and rotate cap to release pellets into cap.
- Unscrew cap and without touching pellets tip them into the mouth under the tongue.
- Allow to dissolve
- Take 15 minutes before meals.

QUESTIONS

Questions?: info@gunainc.com
tel. (484) 223-3500

DOSAGE AND ADMINISTRATION

Take 15 minutes before meals.

- Adults and children twelve years and older: 5 pellets 3 times per day
- Children between 12 years and 6 years of age: 3 pellets 3 times per day
- Children under 6 years: 1 pellet 3 times per day to be dissolved into a little water

Inactive ingredient: Sucrose.